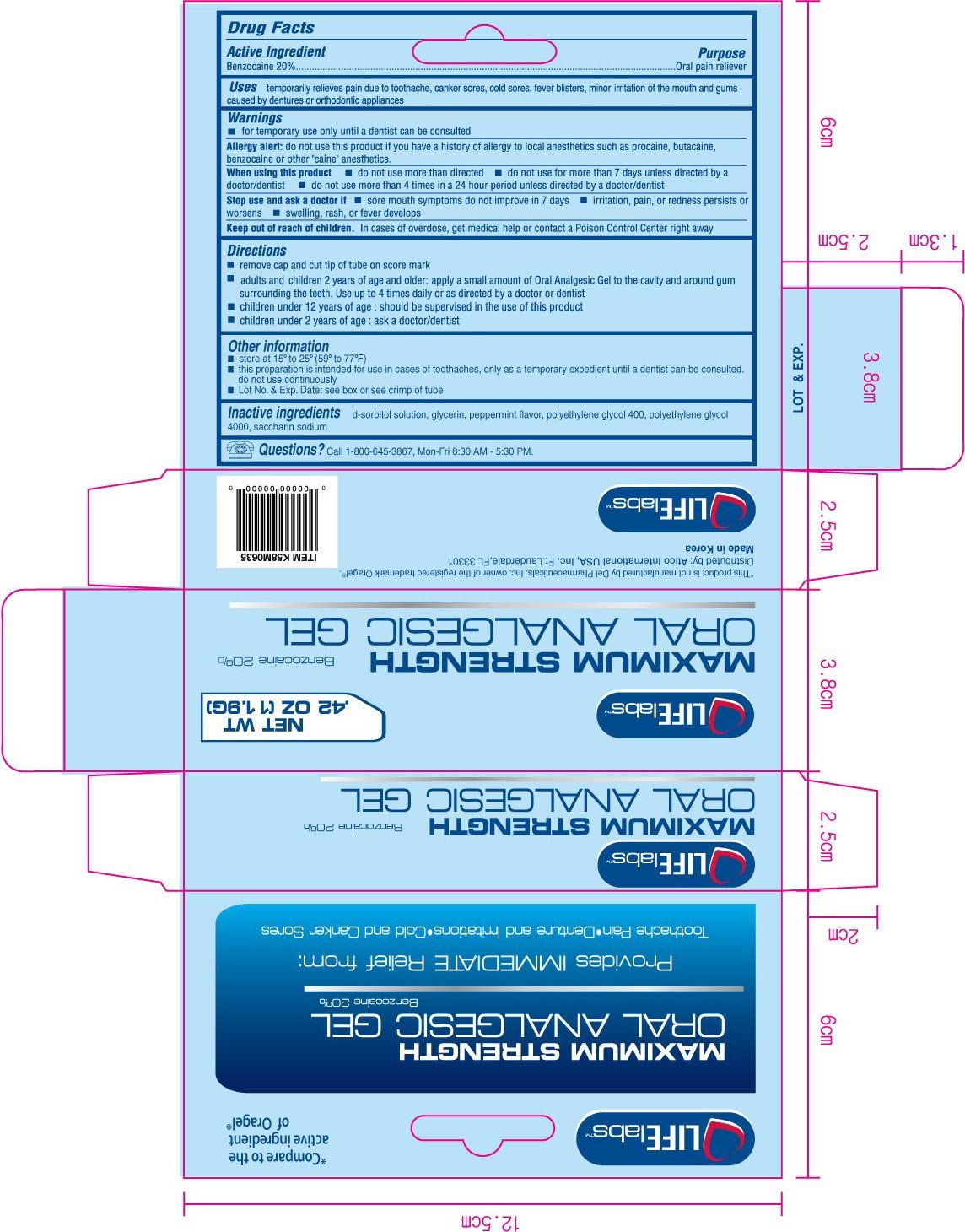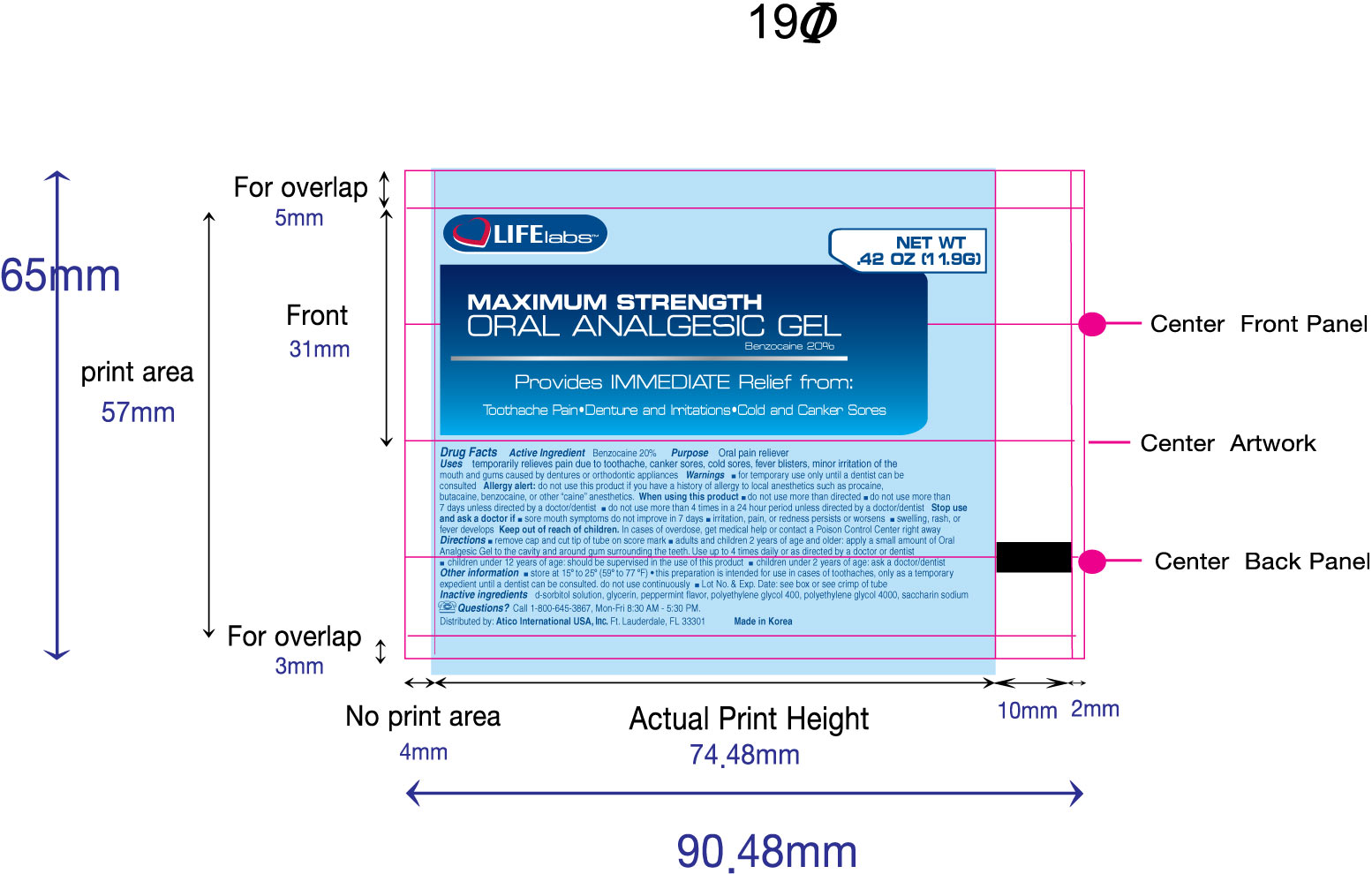 DRUG LABEL: Oral Analgesic
NDC: 51852-101 | Form: GEL
Manufacturer: LIFElabs, a Division of Atico International USA, INC.
Category: otc | Type: HUMAN OTC DRUG LABEL
Date: 20100817

ACTIVE INGREDIENTS: Benzocaine 200 mg/1 g
INACTIVE INGREDIENTS: Sorbitol; Glycerin; Peppermint; Polyethylene Glycol 400; Polyethylene Glycol 4000; Saccharin Sodium

LIFElabs, a Division of Atico International USA, INC.

Oral Analgesic (Maximum Strength)

Active Ingredient

Benzocaine 20%

Purpose

Oral pain reliever

Uses

temporarily relieves pain due to toothache, canker sores, cold sores, fever blisters, minor irritation of the mouth and gums caused by dentures or orthodontic appliances

Warnings

for temporary use only until a dentist can be consulted

Allergy alert:

do not use this product if you have a history of allergy to local anesthetics such a procaine, butacaine, benzocaine or other "caine" anesthetics.

When using this product

- do not use more than directed
- do not use for more than 7 days unless directed by a doctor/dentist
- do not use more than 4 times in a 24 hour period unless directed by a doctor/dentist

Stop use and ask a doctor if

- sore mouth symptoms do not improve in 7 days
- irritation, pain, or redness persists or worsens
- swelling, rash, or fever develops

Keep out of reach of children.

In cases of overdose, get medical help or contact a Poison Control Center right away.

Directions

- remove cap and cut tip of tube on score mark
- adults and children 2 years of age and older: apply a small amount of Oral Analgesic Gel to the cavity and around gum surrounding the teeth. use up to 4 times daily or as directed by a doctor or dentist.
- children under 12 year of age: should be supervised in the use of this product
- children under 2 years of age: ask a doctor/dentist

Other information

- store at 15o to 25o (50o to 77oF)
- This preparation is intended for use in cases of toothaches, only as a temporary expedient until a dentist can be consulted. Do not use continuously
- Lot No. and Exp. Date: see box or see crimp of tube

Inactive Ingredients

d-sorbitol solution, glycerin, peppermint flavor, polyethylene glycol 400, polyethylene glycol 4000, saccharin sodium

Questions?

Call 1-800-645-3867, Mon-Fri 8:30 AM - 5:30 PM.